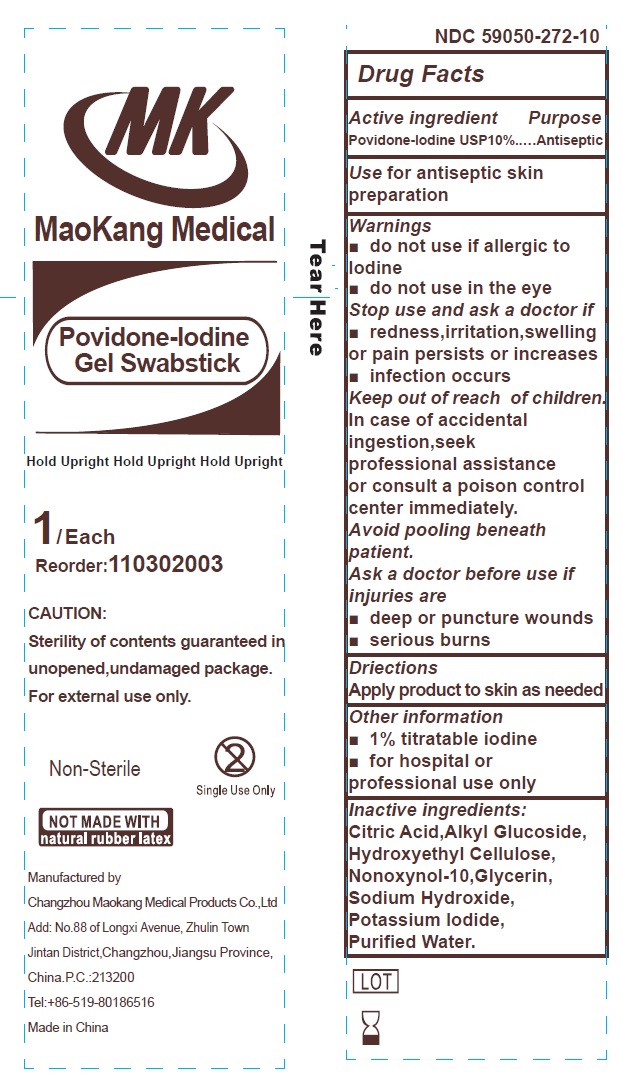 DRUG LABEL: Maokang Medical 10 Povidone Iodine
NDC: 59050-272 | Form: SOLUTION
Manufacturer: Changzhou Maokang Medical Products Co., Ltd
Category: otc | Type: HUMAN OTC DRUG LABEL
Date: 20240719

ACTIVE INGREDIENTS: POVIDONE-IODINE 100 mg/1 mL
INACTIVE INGREDIENTS: CITRIC ACID MONOHYDRATE; HYDROXYETHYL CELLULOSE, UNSPECIFIED; NONOXYNOL-10; GLYCERIN; SODIUM HYDROXIDE; POTASSIUM IODIDE; WATER

Maokang Medical 10% Povidone Iodine Swabsticks

Active ingredient

Povidone-Iodine USP 10%

Purpose

Antiseptic

Use

for antiseptic skin preparation

Warnings

Do not use

- if allergic to Iodine
- do not use in the eye

Stop use and ask a doctor if

- redness,irritation,swelling or pain persists or increases
- infection occurs

Keep out of reach of children.

In case of accidental ingestion,seek professional assistance or consult a poison control center immediately.

Avoid pooling beneath patient.

Ask a doctor before use if injuries are

- deep or puncture wounds
- serious burns

Directions

Apply product to skin as needed

Other information

- 1% titratable iodine
- for hospital or professional use only

Inactive ingredients:

Citric Acid,Alkyl Glucoside,Hydroxyethyl Cellulose,Nonoxynol-10,Glycerin,Sodium Hydroxide,Potassium Iodine,Purified Water.